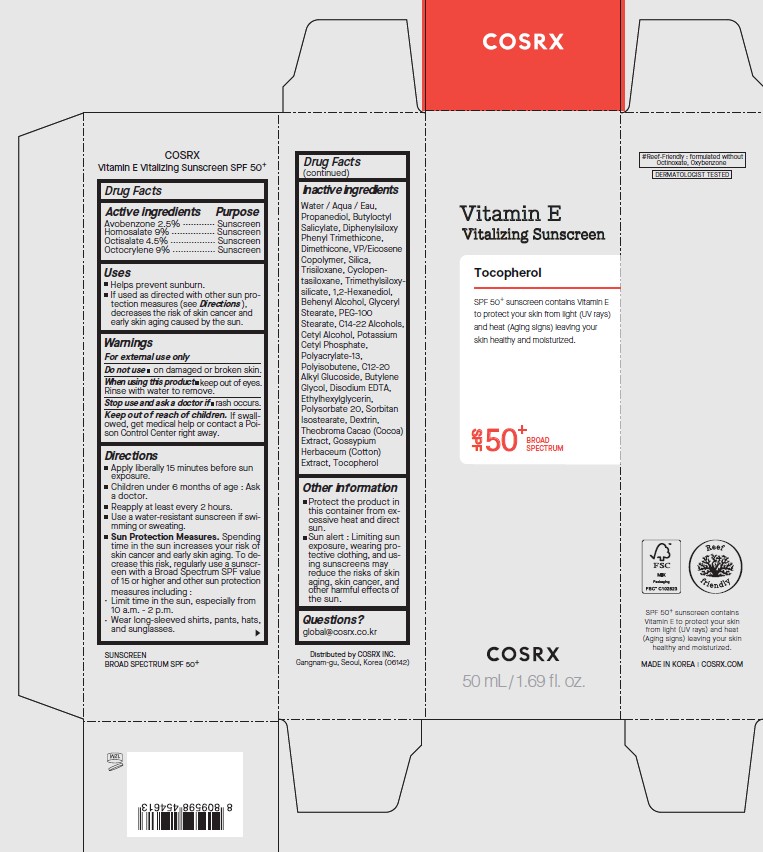 DRUG LABEL: COSRX
NDC: 70319-240 | Form: LOTION
Manufacturer: COSRX inc.
Category: otc | Type: HUMAN OTC DRUG LABEL
Date: 20260113

ACTIVE INGREDIENTS: OCTISALATE 2.25 mg/50 mL; AVOBENZONE 1.25 mg/50 mL; OCTOCRYLENE 4.5 mg/50 mL; HOMOSALATE 4.5 mg/50 mL
INACTIVE INGREDIENTS: CETYL ALCOHOL; ANHYDROUS DEXTROSE; TOCOPHEROL; TRIMETHYLSILOXYSILICATE (M/Q 1.0-1.2); 1,2-HEXANEDIOL; TRISILOXANE; BUTYLOCTYL SALICYLATE; PEG-100 STEARATE; POLYACRYLATE-13; C12-20 ALKYL GLUCOSIDE; BUTYLENE GLYCOL; DIPHENYLSILOXY PHENYL TRIMETHICONE; POLYISOBUTYLENE (45000 MW); CYCLOPENTASILOXANE; BEHENYL ALCOHOL; COCOA; SORBITAN ISOSTEARATE; EDETATE DISODIUM; VINYLPYRROLIDONE/EICOSENE COPOLYMER; C14-22 ALCOHOLS; POLYSORBATE 20; LEVANT COTTON SEED; SILICON DIOXIDE; GLYCERYL STEARATE; POTASSIUM CETYL PHOSPHATE; PROPANEDIOL; WATER; ETHYLHEXYLGLYCERIN; DIMETHICONE

ACTIVE INGREDIENT

Avobenzone 2.5%

Homosalate 9.0%

Octisalate 4.5%

Octocrylene 9.0%

PURPOSE

Sunscreen

INDICATIONS AND USAGE

Helps prevent sunburn.
If used as directed with other sun protection measures (see Directions), decreases the risk of skin cancer and early skin aging caused by the sun.

WARNINGS

For external use only

Do not use on damanged or broken skin.

When using this product keep out of eyes. Rinse with water to remove.

Stop use and ask a doctor if rash occurs.

KEEP OUT OF REACH OF CHILDREN

If swallowed, get medical help or contact a Poison Control Center right away.

OTHER SAFETY INFORMATION

Protect the product in this container from excessive heat and direct sun.
Sun alert : Limiting sun exposure, wearing protective clothing, and using sunscreens may reduce the risks of skin aging, skin cancer, and other harmful effects of the sun.

INACTIVE INGREDIENT

Water / Aqua / Eau,Propanediol, Butyloctyl Salicylate, Diphenylsiloxy Phenyl Trimethicone, Dimethicone, VP/Eicosene Copolymer, Silica, Trisiloxane, Cyclopentasiloxane, Trimethylsiloxysilicate, 1,2-Hexanediol, Behenyl Alcohol, Glyceryl Stearate, PEG-100 Stearate, C14-22 Alcohols, Cetyl Alcohol, Potassium Cetyl Phosphate, Polyacrylate-13, Polyisobutene, C12-20 Alkyl Glucoside, Butylene Glycol, Disodium EDTA, Ethylhexylglycerin, Polysorbate 20, Sorbitan Isostearate, Dextrin, Theobroma Cacao (Cocoa) Extract, Gossypium
Herbaceum (Cotton) Extract, Tocopherol

QUESTIONS

global@cosrx.co.kr

DOSAGE AND ADMINISTRATION

Apply liberally 15 minutes before sun exposure
Children under 6 months of age : Ask a doctor.
Reapply at least every 2 hours.
Use a water-resistant sunscreen if swimming or sweating.
Sun Protection Measures. Spending time in the sun increases your risk of skin cancer and early skin aging. To decrease this risk, regularly use a sunscreen with a Broad Spectrum SPF value of 15 or higher and other sun protection measures including :

Limit time in the sun, especially from 10 a.m. - 2 p.m.

Wear long-sleeved shirts, pants, hats, and sunglasses.

PACKAGE LABEL

Vitamin E

Vitalizing Sunscreen

Tocopherol

SPF 50+ sunscreen contains Vitamin E

to protect your skin from light (UV rays)

and heat (Aging signs) leaving your

skin healthy and moisturized.

SPF50+ BROAD SPECTRUM

50mL /1.69 fl. oz.

COSRX